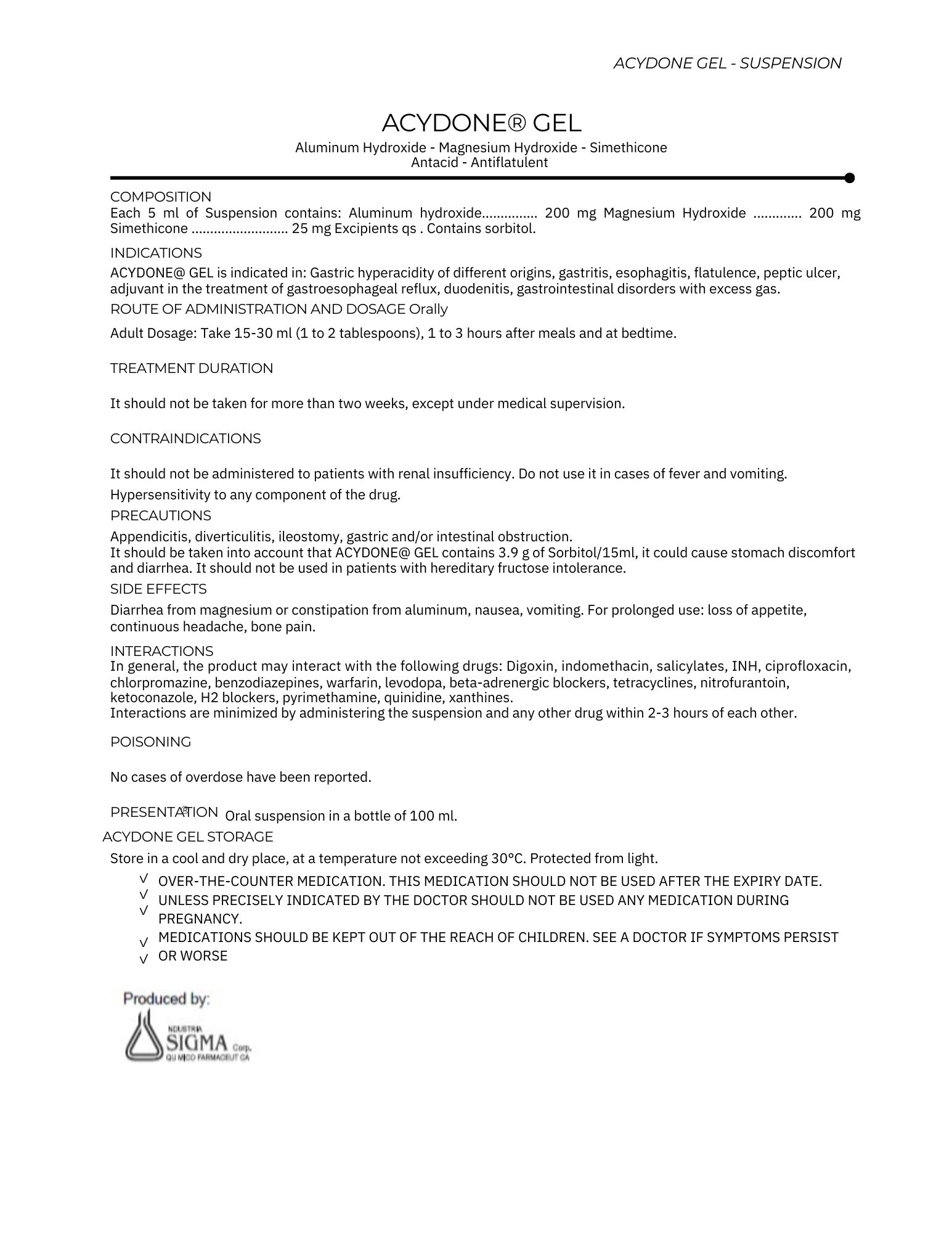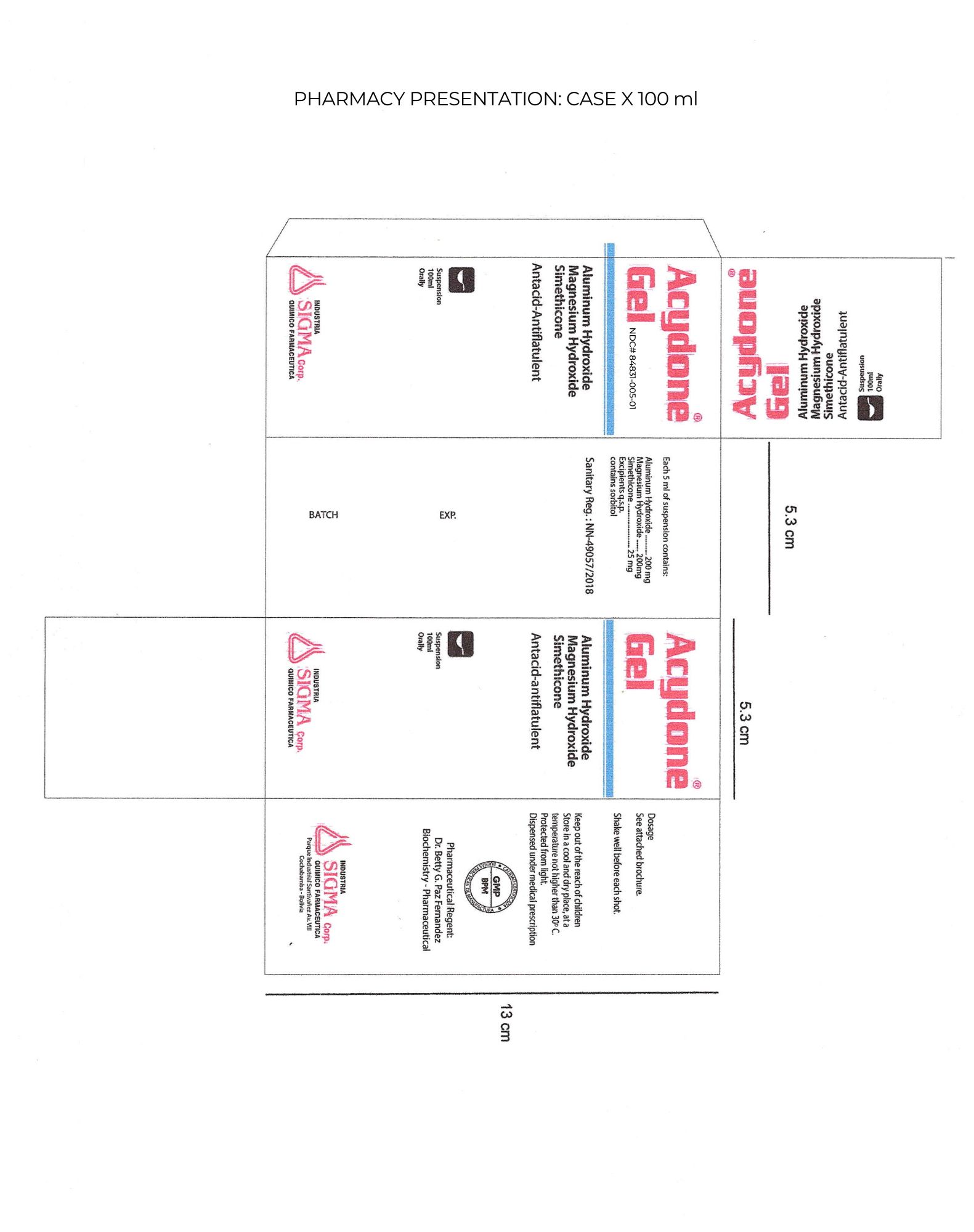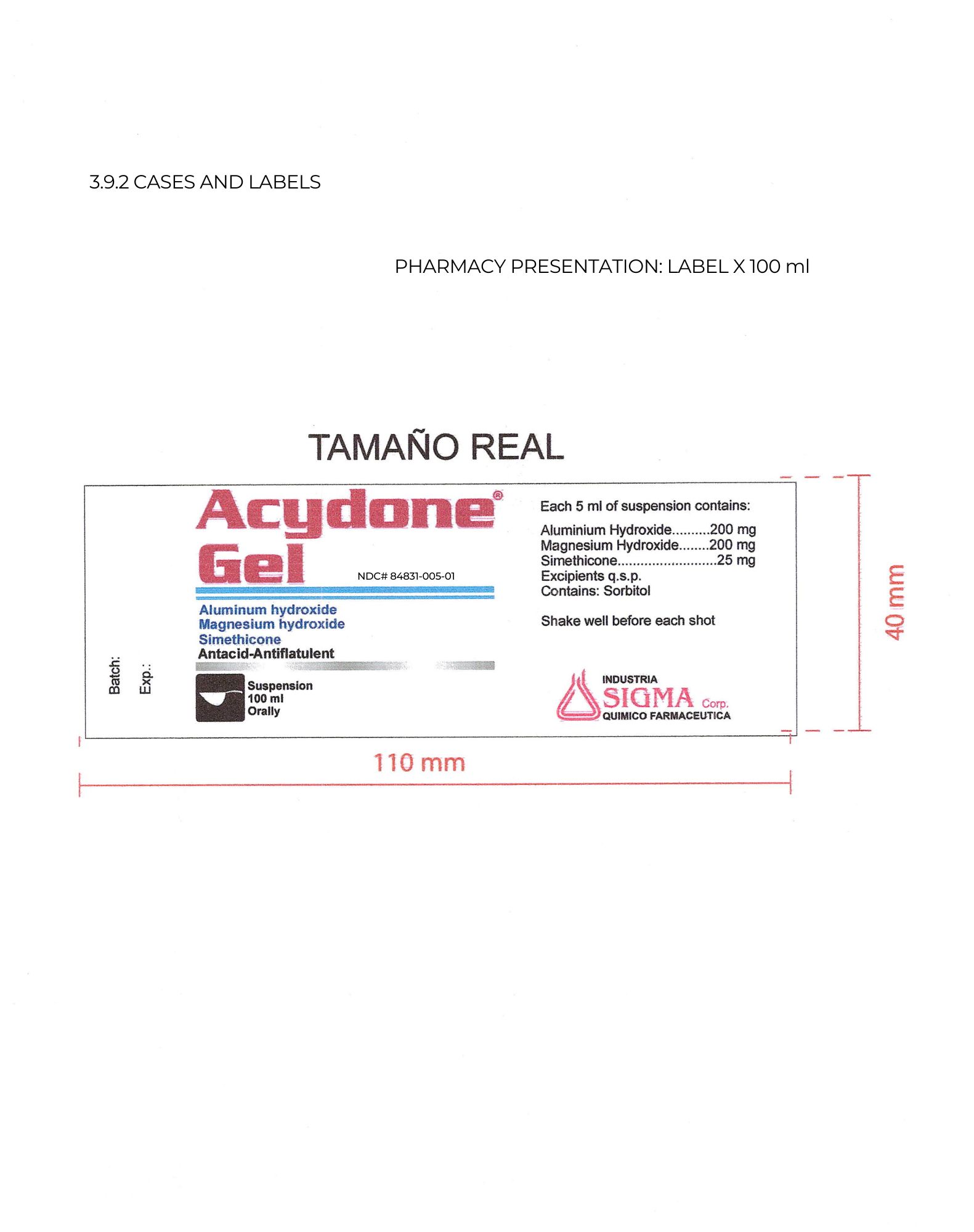 DRUG LABEL: Acydone
NDC: 84831-005 | Form: LIQUID
Manufacturer: Sigma
Category: otc | Type: HUMAN OTC DRUG LABEL
Date: 20241101

ACTIVE INGREDIENTS: DIMETHICONE 25 mg/5000 mg; ALUMINUM HYDROXIDE 200 mg/5000 mg; MAGNESIUM HYDROXIDE 200 mg/5000 mg
INACTIVE INGREDIENTS: PROPYLPARABEN 1 mg/5000 mg; MINT 0.25 mg/5000 mg; ALCOHOL 40 mg/5000 mg; WATER 3558.3 mg/5000 mg; CHERRY 2.5 mg/5000 mg; GLYCERIN 500 mg/5000 mg; ANHYDROUS CITRIC ACID 0.45 mg/5000 mg; METHYLPARABEN 5 mg/5000 mg; XANTHAN GUM 17.5 mg/5000 mg; SORBITOL 400 mg/5000 mg; SODIUM SACCHARIN 50 mg/5000 mg

Active Ingredient

Active ingredient (In each 5 ML Teaspoonful) Purpose
Aluminium Hydroxide 200 mg Antacid
Magnesium Hydroxide 200 mg Antacid
Simeticone 25 mg Anti-gas

Indications and Usage

COMPOSITION Each 5 ml of Suspension contains:
Aluminum hydroxide………..…. 200 mg antacid
Magnesium Hydroxide ............. 200 mg antacid
Simethicone ………………….…. 25 mg antiflatulence
ACYDONE@ GEL is indicated in: Gastric hyperacidity of different origins, gastritis, esophagitis, flatulence, peptic ulcer, adjuvant in the treatment of gastroesophageal reflux, duodenitis, gastrointestinal disorders with excess gas.

Purpose

Use For The Following:
Relief *Acid Indigestion *Heartburn * Sour Stomach * The Symptoms referred to as gas

Warning

Ask a Doctor if you have:

*kidney disease * a magnesium restricted diet * fever *vomiting * fructose intolerance

Ask a Doctor or pharmacist before use if you are taking a prescription drug. Antacid may interact with certain prescription drugs.

Pregnant/Breastfeeding

If pregnant or breast-feeding. Ask a health professional before use.

Children

keep out of reach of children

Directions

Shake well before use * Adults and children 12 years of age and older: take 10 ml to 20 ml (2 to 4 teaspoonfuls) between meals, at bed time or as directed by a doctor * Do not take more than 24 teaspoonful in 24 hours. Take Orally.

Other Information

Keep tightly closed *Protect from feezing * do not use after the expiration date *store less than 86 ° F * ask a doctor if symptoms persist

Inactive Ingredients

Sodium saccharin, Sorbitol 70%, Methylparaben, Propylparaben, flavor, Anhydrous citric acid, ethyl alcohol, Xanthan gum, Glycerine, purified water

RECENT MAJOR CHANGES

changed the title to indications and usage instead of directions.
Added the dosage and administrations sections.